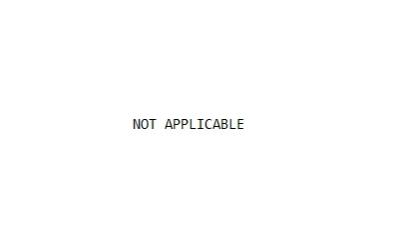 DRUG LABEL: Bc2371 rDNA construct on chromosome 3p1.1-2 in R69 New Zealand white rabbits
NDC: 86047-107 | Form: NOT APPLICABLE
Manufacturer: LFB USA, Inc.
Category: other | Type: INTENTIONAL ANIMAL GENOMIC ALTERATION LABEL
Date: 20250702

ACTIVE INGREDIENTS: BC2371 RDNA CONSTRUCT ON CHROMOSOME 3P1.1-2 IN R69 NEW ZEALAND WHITE RABBITS 1 [arb'U]/1 [arb'U]

Bc2371 rDNA

Bc2371 rDNA CONSTRUCT IN R69 NEW ZEALAND WHITE RABBITS

LFB USA, Inc.

Bc2371 rDNA construct in R69 New Zealand white rabbits, expressing recombinant human Factor VII (rhFVII in the mammary gland).

Heritable construct

1. DESCRIPTION

A single copy of the rDNA construct (designated Bc2371) for human Factor VII (hFVII) has been integrated into the genome, on chromosome 3p1.1-2, of a specific, diploid line (designated R69) of hemizygous and homozygous New Zealand white rabbits (Oryctolagus cuniculus). This rDNA construct includes a chicken β-globin insulator sequence, the goat β-casein promoter at its 5’ end, and the goat β-casein sequences at its 3’ end. The integrated rDNA construct drives the expression of the rhFVII protein in the milk of R69 rabbits. The milk obtained from these rabbits is processed in order to purify and activate the rhFVII to rhFVIIa, which is then intended for use as a therapeutic for human hemophilia A or B patients with inhibitors to Factors VIII and IX.

2. WARNINGS AND PRECAUTIONS

R69 rabbits, or any materials derived from R69 rabbits, are not intended to enter the human or animal food supply.

3. EFFECTIVENESS

Multiple generations of the R69 line have demonstrated genetic stability as established through genetic tests for the presence of the Bc2371 rDNA construct, Bc2371 rDNA sequence fidelity, and Bc2371 construct integration site consistency. For each generation, phenotypic stability has been established based on the presence of recombinant hFVII zymogen in the milk of R69 line rabbits.

4. ANIMAL SAFETY

The health monitoring program for the rabbit population at the LFB USA’s facility follows standardized operation procedures. The testing program characterizing the Specific Pathogen Free (SPF) status of the colony has been instituted based in part on the Federation of European Laboratory Animal Science Associations (FELASA) health monitoring recommendations, and in part on a European Note for Guidance on production and quality. The SPF health screening is performed as a health monitoring (modified sentinel testing) program and is performed on an established schedule (i.e. monthly at a minimum) to include animals that are statistically representative of the entire colony and population (sex, age). Established procedures govern action and any follow-up response to the CVM in the event of confirmed positive results for agents on the SPF exclusion list.

Quarterly morbidity and mortality summaries are prepared and evaluated based on daily health observations of LFB USA’s rabbits colony. The morbidity (see Table 1 below) and mortality (see Table 2 below) provide a data summary for R69 lineage genetically engineered (GE) and wild type rabbits or non genetically engineered rabbit (non-GE) at the facility.

Table 1. Quarterly morbidity summary for Q1-Q4 2017 (Prevalence^1) in genetically engineered (GE) and non-GE rabbits.
 | 2017 Q1 |  | 2017 Q2 |  | 2017 Q3 |  | 2017 Q4
GE status of rabbits | GE | Non-GE | GE | Non-GE | GE | Non-GE | GE | Non-GE
Rolling Population | 680 | 106 | 654 | 100 | 687 | 100 | 753 | 111
Morbidity Cases (Integument)^2 | 113 | 6 | 81 | 2 | 90 | 6 | 117 | 5
Morbidity Cases (less Integument)^3 | 140 | 33 | 134 | 24 | 160 | 22 | 212 | 19
% Morbidity (less Integument)^4 | 20.6% | 31.1% | 20.5% | 24.0% | 23.3% | 22.0% | 28.2% | 17.1%

^1Prevalence (% Morbidity) is the number new treatment/health cases in rabbits expressed as a percentage of rolling population for that quarter. Note that a rabbit may have more than one new case during a quarter.

^2Total number of new morbidity cases attributed to hair/skin/integument only.

^3Total number of new morbidity cases that include observations related to the following systems/categories: musculoskeletal, respiratory, reproductive, digestive, nervous, mammary, ophthalmic, urinary, behavior, and unthrifty/failure to thrive (integument excluded).

^4% Morbidity (less integumentary) represents the number of new morbidity cases minus those cases attributed to hair/skin/integument expressed as a % of the rolling population for that quarter.

Table 2. Quarterly mortality summary for Q1-Q4 2017 (Prevalence^1) in genetically engineered (GE) and non-GE rabbits.
 | 2017 Q1 |  | 2017 Q2 |  | 2017 Q3 |  | 2017 Q4
GE status of rabbits | GE | Non-GE | GE | Non-GE | GE | Non-GE | GE | Non-GE
Rolling Population | 680 | 106 | 654 | 100 | 687 | 100 | 753 | 111
Mortality Cases^2 | 17 | 1 | 36 | 10 | 27 | 7 | 32 | 3
% Mortality | 2.5% | 0.9% | 5.5% | 10.0% | 3.9% | 7.0% | 4.2% | 2.7%

^1Prevalence (% Mortality) is the number of animals that died or were euthanized for cause in a period expressed as a percentage of rolling population for that quarter.

^2Table captures mortalities due to spontaneous death and euthanasia for untreatable and serious health conditions (musculoskeletal, central nervous, ophthalmic, respiratory, urinary, and unthrifty/failure to thrive). Mortality in the table do not include euthanasia for purposes of routine colony population management purposes.

The rolling population, as captured in Tables 1 and 2 above, is the average of the monthly census for the facility for that quarter. The end of the month census is the total animal count the last day of the month but does not include kits who have not weaned. Therefore prevalence (% Morbidity) is the number of animals with new health cases in a period expressed as a percentage of the rolling population for a particular quarter. Table 2 for mortality does not include healthy rabbits submitted for SPF health screening purposes. Note that the facility population primarily consists of GE rabbits.

Even though the level of observation of GE production rabbits vs. non-GE rabbits was more rigorous, primarily due to the more intense nature of the reproductive and milking procedures (non-GE does were not machine milked) morbidity and mortality comparisons between GE and non-GE rabbits at the facility demonstrated a lack of adverse effect for the rDNA construct or its expression product.

5. LIMITATIONS OF USE

The R69 line of New Zealand white rabbits in the United States must be housed in only the LFB USA, Inc. facilities specified in the approved application.

Manufactured by:
LFB USA
175 Crossing Boulevard
Framingham, MA 01702

Approved by FDA under NADA 141-511